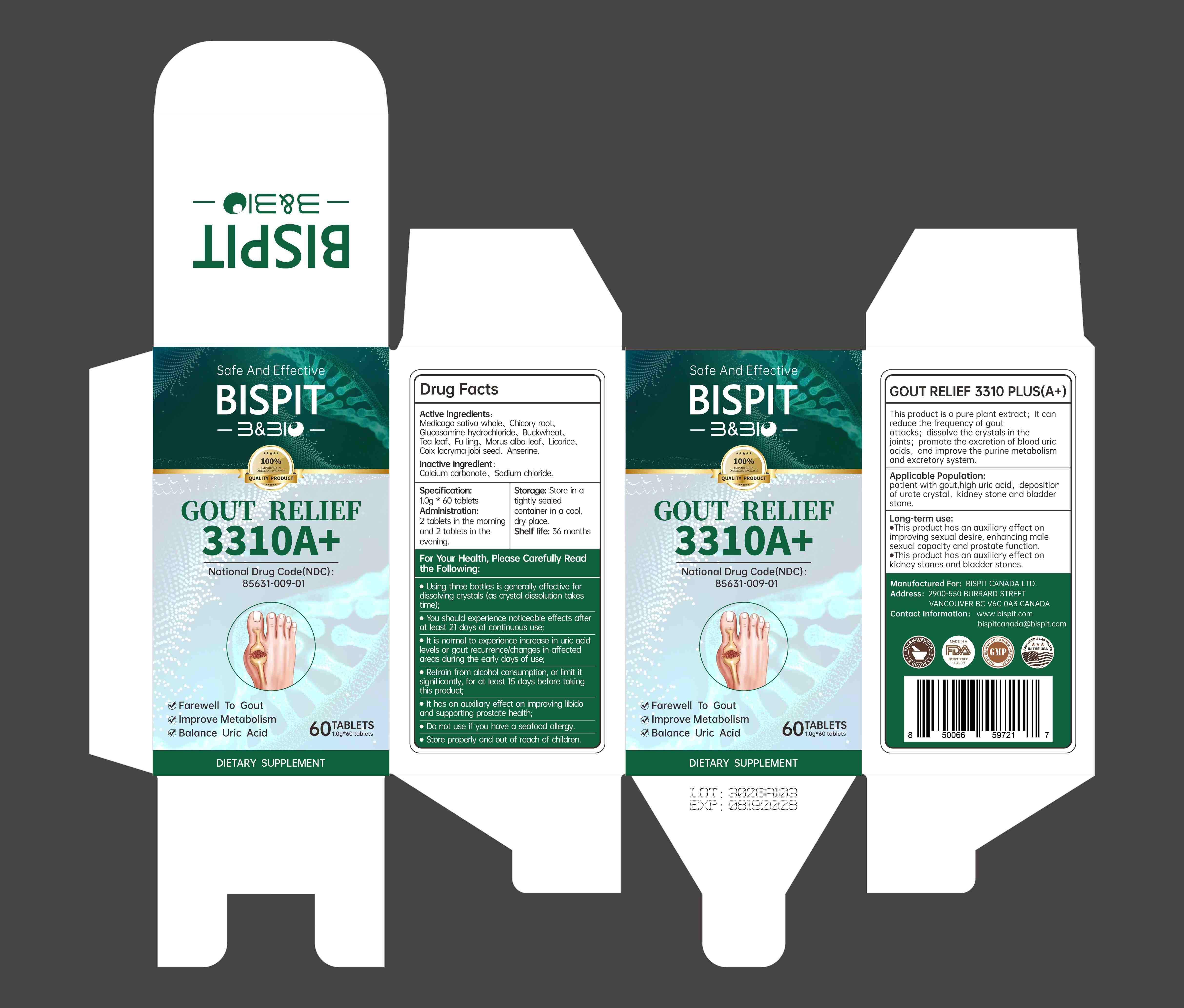 DRUG LABEL: Gout Relief 3310A Plus
NDC: 85631-009 | Form: TABLET
Manufacturer: Bispit Canada Ltd.
Category: homeopathic | Type: HUMAN OTC DRUG LABEL
Date: 20250906

ACTIVE INGREDIENTS: LICORICE 1 mg/1 g; MEDICAGO SATIVA WHOLE 150 mg/1 g; BUCKWHEAT 40 mg/1 g; FU LING 10 mg/1 g; CHICORY ROOT 180 mg/1 g; MORUS ALBA LEAF 75 mg/1 g; ANSERINE 350 mg/1 g; TEA LEAF 34 mg/1 g; COIX LACRYMA-JOBI SEED 40 mg/1 g; GLUCOSAMINE HYDROCHLORIDE 70 mg/1 g
INACTIVE INGREDIENTS: CALCIUM CARBONATE; SODIUM CHLORIDE

ACTIVE INGREDIENT

MEDICAGO SATIVA WHOLE
CHICORY ROOT
GLUCOSAMINE HYDROCHLORIDE
BUCKWHEAT
TEA LEAF
MORUS ALBA LEAF
LICORICE
FU LING
COIX LACRYMA-JOBI SEED
ANSERINE

INACTIVE INGREDIENT

CALCIUM CARBONATE
SODIUM CHLORIDE

WARNINGS

Ulsing three bottles is generally effective fordissolving crystals (as crystal dissoiution takestime);
You should experience noticeable effects afterat least 21 days of conbnlous use,It is noral to experence increose in uric acidlevels or gout recurrencelchanges imn affectedareas during the early days of use;Refrain from olcohol consumption, or limit itsionificantly, for at least 15 days before takingthis product;
lt has an auxiliary effect on improving libidoand supporting prostate health,
Do not use if you have a seafood allergy.
Store properly and out of reach of children.

Store properly and out of reach of children.

PURPOSE

This product is a pure plant extract; it canreduce the frequency of goutattacks; dissolve the crystals in thejoints; promote the excretion of blood uricacids,andimprove the purine metabolismand excretory system.

DOSAGE AND ADMINISTRATION

2 tablets in the momingand 2 toblets in the evening.

INDICATIONS AND USAGE

Applicable Population:patient with gout,high uric acid, depositionof urate crystal, kidney stone and bladder
stone.